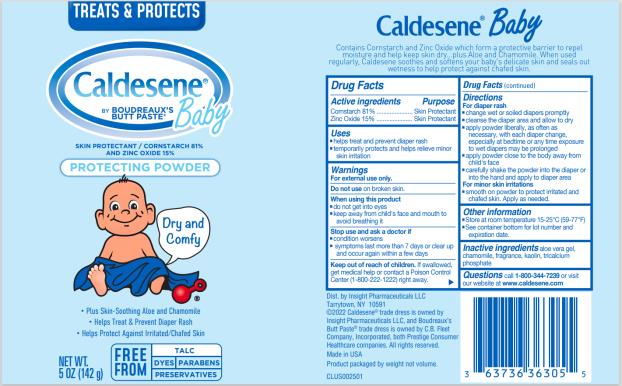 DRUG LABEL: Caldesene Baby
NDC: 63736-305 | Form: POWDER
Manufacturer: Insight Pharmaceuticals LLC
Category: otc | Type: HUMAN OTC DRUG LABEL
Date: 20240129

ACTIVE INGREDIENTS: STARCH, CORN 115 g/142 g; ZINC OXIDE 21 g/142 g
INACTIVE INGREDIENTS: ALOE VERA LEAF; CHAMOMILE; KAOLIN; TRICALCIUM PHOSPHATE

Caldesene Baby Powder 636736-305

Caldesene®
Baby

Drug Facts

Active ingredients

Cornstarch 81%

Zinc Oxide 15%

Purpose

Skin Protectant

Skin Protectant

Uses

- helps treats and prevents diaper rash
- temporarily protects and helps relieve minor skin irritation

Warnings

For external use only.

Do not use

on broken skin.

When using this product

- do not get into eyes
- keep away from child's face and mouth to avoid breathing it

Stop use and ask a doctor if

- condition worsens
- symptoms last more than 7 days or clear up and occur again within a few days

Keep out of reach of children.

If swallowed, get medical help or contact a Poison Control Center (1-800-222-1222) right away.

Directions

For diaper rash

- change wet or soiled diapers promptly
- cleanse the diaper area and allow to dry
- apply powder liberally, as often as necessary, with each diaper change, especially at bedtime or anytime exposure to wet diapers may be prolonged
- apply powder close to the body away from child's face
- carefully shake the powder into the diaper or into the hand and apply to diaper area

For minor skin irritations

- smooth on powder to protect irritated and chafed skin. Apply as needed.

Other information

- Store at room temperature 15°–25°C (59°–77°F).
- See container bottom for lot number and expiration date.

Inactive ingredients

aloe vera gel, chamomile, fragrance, kaolin, tricalcium phosphate

Questions?

1-800-344-7239 or visit our website at www.caldesene.com

PRINCIPAL DISPLAY PANEL - 142 g Label

Caldesene®
Baby

Skin Protectant / Cornstarch Powder 18%
and Zinc Oxide 15%

NET WT 5 OZ (142 g)